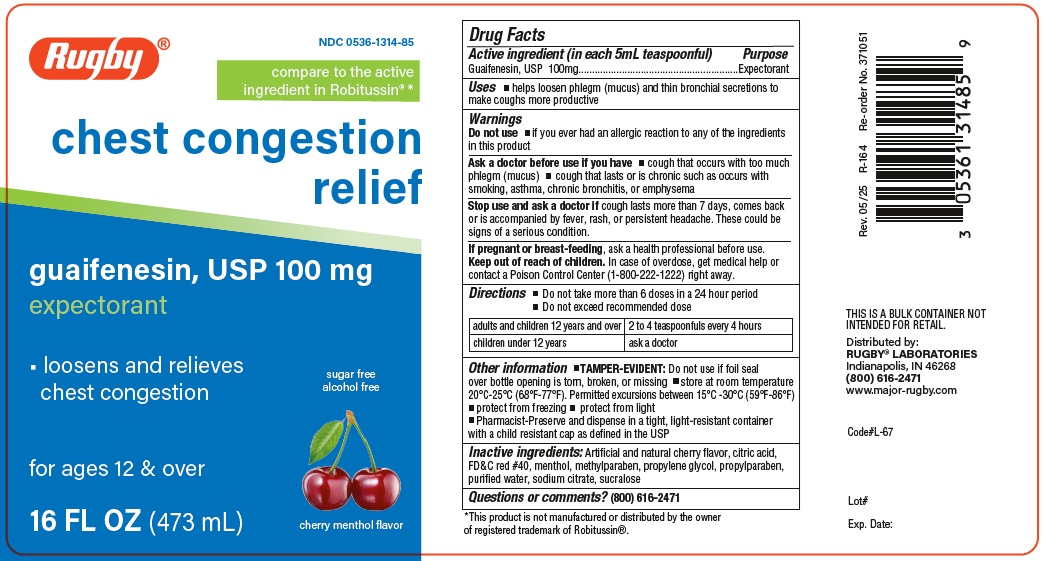 DRUG LABEL: Chest Congestion Relief
NDC: 0536-1314 | Form: LIQUID
Manufacturer: RUGBY LABORATORIES
Category: otc | Type: HUMAN OTC DRUG LABEL
Date: 20251230

ACTIVE INGREDIENTS: GUAIFENESIN 100 mg/5 mL
INACTIVE INGREDIENTS: ANHYDROUS CITRIC ACID; FD&C RED NO. 40; MENTHOL; METHYLPARABEN; PROPYLENE GLYCOL; PROPYLPARABEN; WATER; SODIUM CITRATE; SUCRALOSE

Rugby- Chest Cong 1314

Active ingredients

Guaifenesin 100 mg

Purpose

Expectorant

Uses

helps lossen phlegm (mucus) and thin bronchial secretions to make coughs more productive

Warnings

Do not useif you ever had an allergic reaction to any of the indregients in this product

Ask a doctor before use if you have

- cough that occurs with too much phlegm (mucus)
- cough that lasts or is chronic such as occurs with smoking, asthma, chronic bronchitis, or emphysema

Stop use and ask a doctor ifcough lasts more than 7 days, comes back or is accompanied by fever, rash, or persistent headache. These could be signs of a serious condition.

PREGNANCY OR BREAST FEEDING

If pregnant or breast feeding, ask a health professional before use.

Keep out of reach of children. In case of overdose, get medical help or contact a Poison Control Center (1-800-222-1222) right away.

Directions

- Do not take more than 6 doses in a 24 hour period
- Do not exceed recommended dose

Adults and children 12 years and over | 2 to 4 teaspoonfuls every 4 hours
children under 12 years | ask a doctor

INACTIVE INGREDIENT

Inactive ingredients. Artificial and natural cherry flavor, citric acid, FD&C Red #40, menthol, methylparaben, propylene glycol, propylparaben water, sodium citrate, sucralose

Questions or comments? 1-800-645-2158